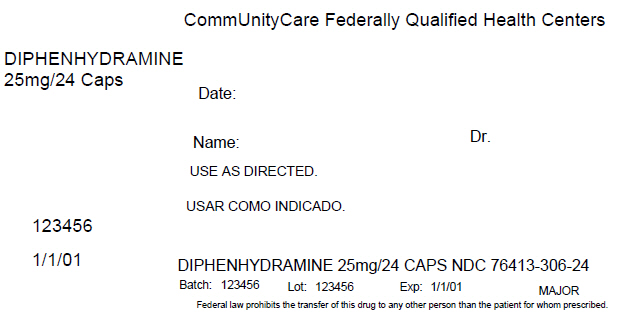 DRUG LABEL: Diphenhydramine hydrochloride
NDC: 76413-306 | Form: CAPSULE
Manufacturer: Central Texas Community Health Centers
Category: otc | Type: HUMAN OTC DRUG LABEL
Date: 20160322

ACTIVE INGREDIENTS: DIPHENHYDRAMINE HYDROCHLORIDE 25 mg/1 1
INACTIVE INGREDIENTS: BUTYLPARABEN; D&C RED NO. 28; FD&C BLUE NO. 1; GELATIN; LACTOSE, UNSPECIFIED FORM; MAGNESIUM STEARATE; METHYLPARABEN; PROPYLPARABEN; POLYSORBATE 80

Diphenhydramine hydrochloride

Active ingredient (in each banded capsule)

Diphenhydramine HCl 25 mg

Purpose

Antihistamine

Uses

- temporarily relieves these symptoms due to hay fever or other upper respiratory allergies:
  - runny nose
  - sneezing
  - itchy, watery eyes
  - itching of the nose or throat
- temporarily relieves these symptoms due to the common cold:
  - runny nose
  - sneezing

Warnings

Do not use

- to make a child sleepy
- with any other product containing diphenhydramine, even one used on skin

Ask a doctor before use if you have

- a breathing problem such as emphysema or chronic bronchitis
- glaucoma
- trouble urinating due to an enlarged prostate gland

Ask a doctor or pharmacist before use if you are

taking sedatives or tranquilizers.

When using this product

- marked drowsiness may occur
- avoid alcoholic drinks
- alcohol, sedatives, and tranquilizers may increase drowsiness
- be careful when driving a motor vehicle or operating machinery
- excitability may occur, especially in children

If pregnant of breast-feeding,

ask a health professional before use.

Keep out of reach of children.

In case of overdose, get medical help or contact a Poison Control Center right away.

Directions

- take every 4 to 6 hours
- do not take more than 6 doses in 24 hours

adults and children 12 years of age and over | 1 to 2 capsules
children 6 to under 12 years of age | 1 capsule
children under 6 years of age | do not use this product in children under 6 years of age

Other information

- store at 25ºC (77ºF); excursions permitted between 15º-30ºC (59º-86ºF)
- see end flap for expiration date and lot number
- protect from moisture

Inactive ingredients

butylparaben, corn starch, D&C red #28, edible ink, FD&C blue #1, FD&C red #40, gelatin, lactose, magnesium stearate, methylparaben, polysorbate 80, propylparaben, silica gel

Questions or comments?

1-800-616-2471

PRINCIPAL DISPLAY PANEL - 25 mg Capsule Blister Pack Carton Label

CommUnityCare Federally Qualified Health Centers

DIPHENHYDRAMINE
25mg/24 Caps

Date:

Name:
Dr.

USE AS DIRECTED.

123456

1/1/01

DIPHENHYDRAMINE 25mg/24 CAPS NDC 76413-306-24

Batch: 123456
Lot: 123456
Exp: 1/1/01
MAJOR

Federal law prohibits the transfer of this drug to any other person than the patient for whom prescribed.